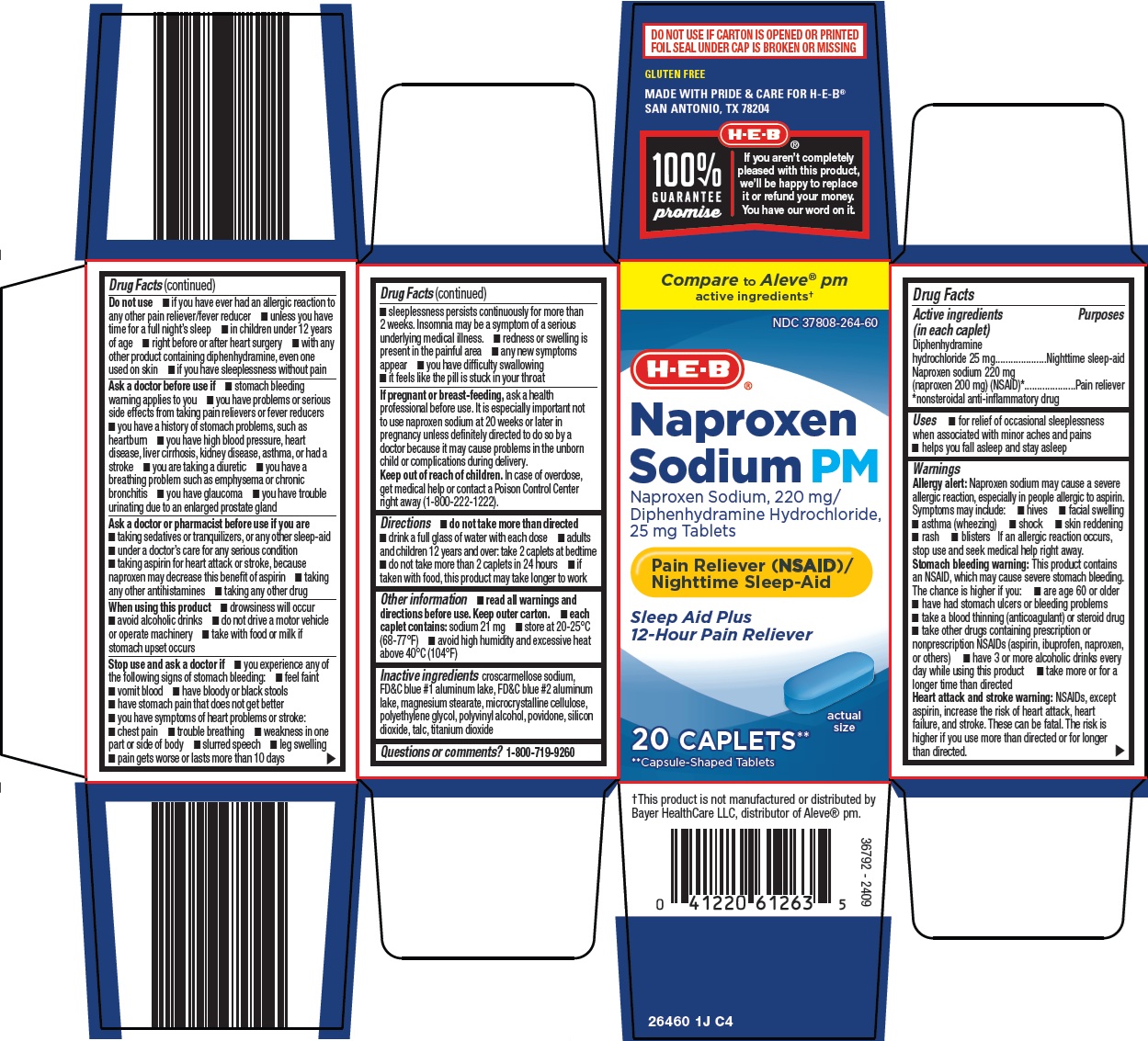 DRUG LABEL: naproxen sodium pm
NDC: 37808-264 | Form: TABLET, FILM COATED
Manufacturer: H E B
Category: otc | Type: HUMAN OTC DRUG LABEL
Date: 20260212

ACTIVE INGREDIENTS: DIPHENHYDRAMINE HYDROCHLORIDE 25 mg/1 1; NAPROXEN SODIUM 220 mg/1 1
INACTIVE INGREDIENTS: CROSCARMELLOSE SODIUM; FD&C BLUE NO. 1 ALUMINUM LAKE; FD&C BLUE NO. 2 ALUMINUM LAKE; MAGNESIUM STEARATE; MICROCRYSTALLINE CELLULOSE; POLYETHYLENE GLYCOL, UNSPECIFIED; POLYVINYL ALCOHOL, UNSPECIFIED; POVIDONE, UNSPECIFIED; SILICON DIOXIDE; TALC; TITANIUM DIOXIDE

HEB Naproxen Sodium PM Drug Facts

Active ingredients (in each caplet)

Diphenhydramine hydrochloride 25 mg

Naproxen sodium 220 mg (naproxen 200 mg) (NSAID)*

*nonsteroidal anti-inflammatory drug

Purposes

Nighttime sleep-aid

Pain reliever

Uses

- for relief of occasional sleeplessness when associated with minor aches and pains
- helps you fall asleep and stay asleep

Warnings

Allergy alert: Naproxen sodium may cause a severe allergic reaction, especially in people allergic to aspirin.

Symptoms may include:

- hives
- facial swelling
- asthma (wheezing)
- shock
- skin reddening
- rash
- blisters

If an allergic reaction occurs, stop use and seek medical help right away.

Stomach bleeding warning: This product contains an NSAID, which may cause severe stomach bleeding. The chance is higher if you:

- are age 60 or older
- have had stomach ulcers or bleeding problems
- take a blood thinning (anticoagulant) or steroid drug
- take other drugs containing prescription or nonprescription NSAIDs (aspirin, ibuprofen, naproxen, or others)
- have 3 or more alcoholic drinks every day while using this product
- take more or for a longer time than directed

Heart attack and stroke warning: NSAIDs, except aspirin, increase the risk of heart attack, heart failure, and stroke. These can be fatal. The risk is higher if you use more than directed or for longer than directed.

Do not use

- if you have ever had an allergic reaction to any other pain reliever/fever reducer
- unless you have time for a full night’s sleep
- in children under 12 years of age
- right before or after heart surgery
- with any other product containing diphenhydramine, even one used on skin
- if you have sleeplessness without pain

Ask a doctor before use if

- stomach bleeding warning applies to you
- you have problems or serious side effects from taking pain relievers or fever reducers
- you have a history of stomach problems, such as heartburn
- you have high blood pressure, heart disease, liver cirrhosis, kidney disease, asthma, or had a stroke
- you are taking a diuretic
- you have a breathing problem such as emphysema or chronic bronchitis
- you have glaucoma
- you have trouble urinating due to an enlarged prostate gland

Ask a doctor or pharmacist before use if you are

- taking sedatives or tranquilizers, or any other sleep-aid
- under a doctor’s care for any serious condition
- taking aspirin for heart attack or stroke, because naproxen may decrease this benefit of aspirin
- taking any other antihistamines
- taking any other drug

When using this product

- drowsiness will occur
- avoid alcoholic drinks
- do not drive a motor vehicle or operate machinery
- take with food or milk if stomach upset occurs

Stop use and ask a doctor if

- you experience any of the following signs of stomach bleeding:
- feel faint
- vomit blood
- have bloody or black stools
- have stomach pain that does not get better
- you have symptoms of heart problems or stroke:
- chest pain
- trouble breathing
- weakness in one part or side of body
- slurred speech
- leg swelling
- pain gets worse or lasts more than 10 days
- sleeplessness persists continuously for more than 2 weeks. Insomnia may be a symptom of a serious underlying medical illness.
- redness or swelling is present in the painful area
- any new symptoms appear
- you have difficulty swallowing
- it feels like the pill is stuck in your throat

If pregnant or breast-feeding,

ask a health professional before use. It is especially important not to use naproxen sodium at 20 weeks or later in pregnancy unless definitely directed to do so by a doctor because it may cause problems in the unborn child or complications during delivery.

Keep out of reach of children.

In case of overdose, get medical help or contact a Poison Control Center right away (1-800-222-1222).

Directions

- do not take more than directed
- drink a full glass of water with each dose
- adults and children 12 years and over: take 2 caplets at bedtime
- do not take more than 2 caplets in 24 hours
- if taken with food, this product may take longer to work

Other information

- read all warnings and directions before use. Keep outer carton.
- each caplet contains: sodium 21 mg
- store at 20-25°C (68-77°F)
- avoid high humidity and excessive heat above 40°C (104°F)

Inactive ingredients

croscarmellose sodium, FD&C blue #1 aluminum lake, FD&C blue #2 aluminum lake, magnesium stearate, microcrystalline cellulose, polyethylene glycol, polyvinyl alcohol, povidone, silicon dioxide, talc, titanium dioxide

Questions or comments?

1-800-719-9260

Package/Label Principal Display Panel

Compare to Aleve® pm active ingredients

H-E-B®

Naproxen Sodium PM

Naproxen Sodium, 220 mg/Diphenhydramine Hydrochloride, 25 mg Tablets

Pain Reliever (NSAID) / Nighttime Sleep-Aid

Sleep Aid Plus 12-Hour Pain Reliever

actual size

20 CAPLETS**

**Capsule-Shaped Tablets